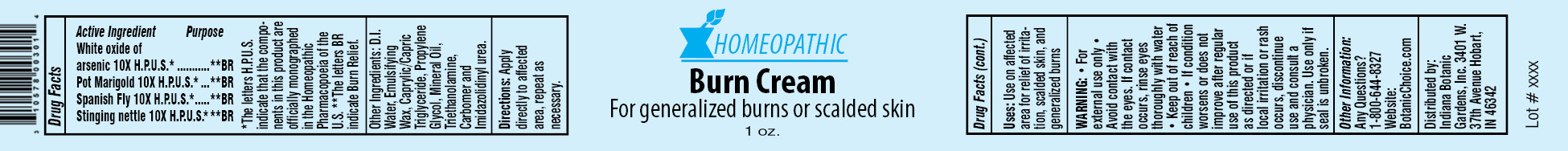 DRUG LABEL: Homeopathic Burn
NDC: 10578-003 | Form: CREAM
Manufacturer: Indiana Botanic Gardens
Category: homeopathic | Type: HUMAN OTC DRUG LABEL
Date: 20120427

ACTIVE INGREDIENTS: ARSENIC TRIOXIDE 10 [hp_X]/28 g; CALENDULA OFFICINALIS FLOWER 10 [hp_X]/28 g; LYTTA VESICATORIA 10 [hp_X]/28 g; URTICA URENS 10 [hp_X]/28 g
INACTIVE INGREDIENTS: WATER; CETOSTEARYL ALCOHOL; POLYSORBATE 60; TRICAPRYLIN; PROPYLENE GLYCOL; MINERAL OIL; TROLAMINE; CARBOMER 934; DIAZOLIDINYL UREA

Homeopathic Burn Cream

Active Ingredients

White oxide of arsenic 10X H.P.U.S.*

Pot Marigold 10X H.P.U.S.*

Spanish Fly 10X H.P.U.S.*

Stinging nettle 10X H.P.U.S.*

Purpose

**BR

**BR

**BR

**BR

*The letters H.P.U.S. indicate that the components in this product are officially monographed in the Homeopathic Pharmacopoeia of the U.S. **The letters BR indicate Burn Relief.

Other Ingredients:

D.I. Water, Emulsifying Wax, Caprylic/Capric Triglyceride, Propylene Glycol, Mineral Oil, Triethanolamine, Carbomer and Imidazolidinyl urea.

Directions:

Apply directly to affected area, repeat as necessary.

Uses:

Use on affected area for relief of irritation, scalded skin, and generalized burns

WARNING:

- for external use only
- Avoid contact with the eyes. If contact occurs, rinse eyes thoroughly with water

- Keep out of reach of children

STOP USE

- If condition worsens or does not improve after regular use of this product as directed or if local irritation or rash occurs, discontinue use and consult a physician.

Use only if seal is unbroken.

Other Information:

Any Questions?

1-800-644-8327

Website:

BotanicChoice.com

Distributed by:

Indiana Botanic Gardens, Inc. 3401 W. 37th Avenue Hobart, IN 46342

Homeopathic Burn Cream

For generalized burns or scalded skin

1 oz.